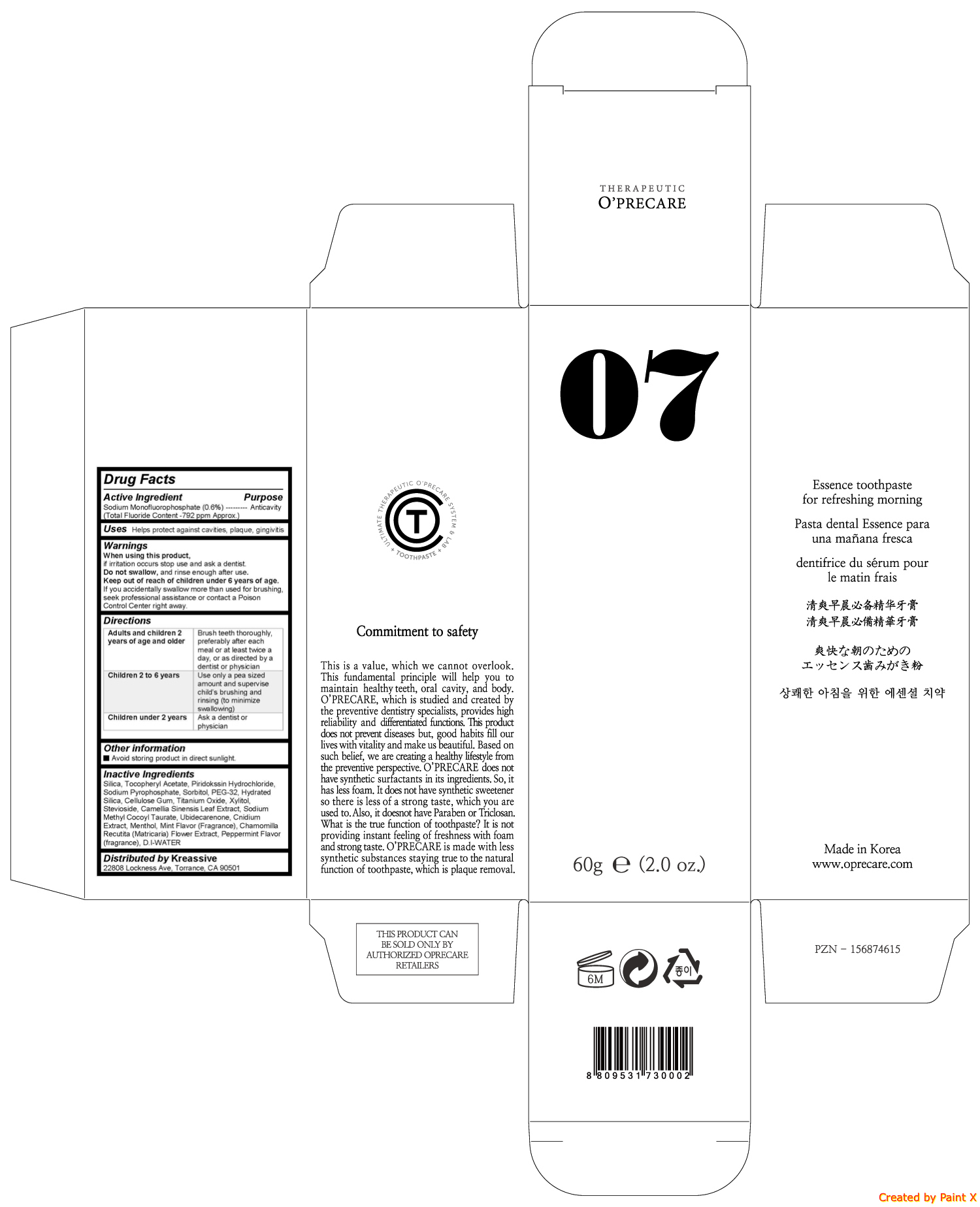 DRUG LABEL: OPRECARE 07
NDC: 71764-100 | Form: PASTE
Manufacturer: O'PRECARE
Category: otc | Type: HUMAN OTC DRUG LABEL
Date: 20171011

ACTIVE INGREDIENTS: SODIUM MONOFLUOROPHOSPHATE 0.36 g/60 g
INACTIVE INGREDIENTS: SILICON DIOXIDE; CARBOXYMETHYLCELLULOSE SODIUM, UNSPECIFIED FORM; XYLITOL; MENTHOL; SODIUM METHYL COCOYL TAURATE; GREEN TEA LEAF; UBIDECARENONE; SODIUM PYROPHOSPHATE; SORBITOL; HYDRATED SILICA; TITANIUM DIOXIDE; STEVIOSIDE; POLYETHYLENE GLYCOL 1500; .ALPHA.-TOCOPHEROL ACETATE; CHAMOMILE

O'PRECARE 07

Active ingredient

Sodium Monofluorophosphate (0.6%)

Purpose

Anticavity

Warnings

When using this product, if irritation occurs stop use and ask a dentist. Do not swallow, and rinse enough after use. Keep out of reach of children under 6 years of age. If you accidentally swallow more than used for brushing, seek professional assistance or contact a Poison Control Center right away.

Uses

Helps protect against cavities, plaque, gingivitis

Directions

Adults and children 2 years of age and older | Brush teeth thoroughly, preferably after each meal or at least twice a day, or as directed by a dentist or physician
Children 2 to 6 years | Use only a pea sized amount and supervise childs brushing and rinsing (to minimize swallowing)
Children under 2 years | Ask a dentist or physician

Keep out of reach of children under 6 years of age. If you accidentally swallow more than used for brushing, seek professional assistance or contact a Poison Control Center right away.

Inactive ingredients

Silica, Tocopheryl Acetate, Piridokssin Hydrochloride, Sodium Pyrophosphate, Sorbitol, PEG-32, Hydrated Silica, Cellulose Gum, Titanium Oxide, Xylitol, Stevioside, Camellia Sinensis Leaf Extract, Sodium Methyl Cocoyl Taurate, Ubidecarenone, Cnidium Extract, Menthol, Mint Flavor (Fragrance), Chamomilla Recutita (Matricaria) Flower Extract, Peppermint Flavor (fragrance), D.I-WATER